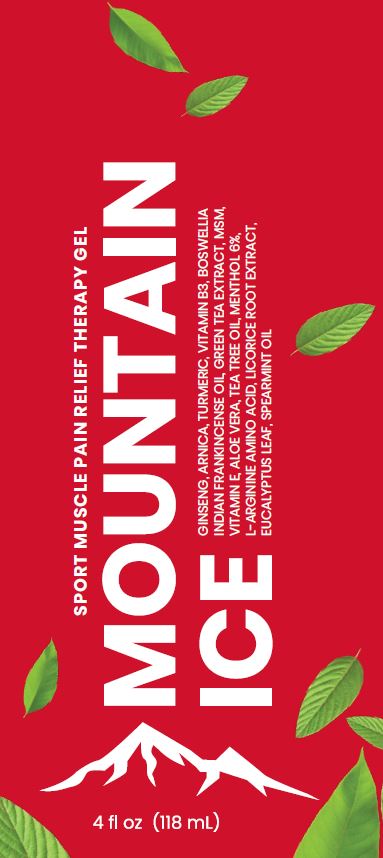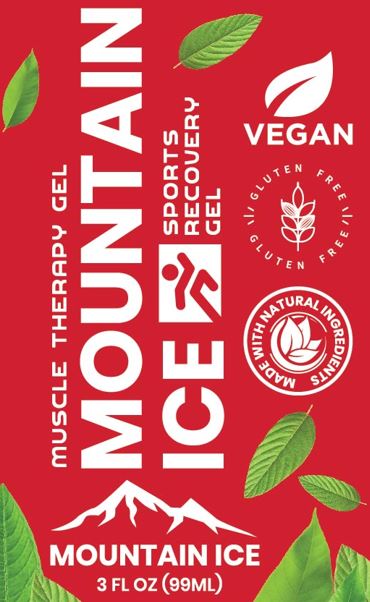 DRUG LABEL: Mountain Ice Sports Recovery
NDC: 72793-201 | Form: GEL
Manufacturer: Mountainside Medical Equipment, Inc.
Category: otc | Type: HUMAN OTC DRUG LABEL
Date: 20251020

ACTIVE INGREDIENTS: MENTHOL, UNSPECIFIED FORM 6 g/100 mL
INACTIVE INGREDIENTS: ALOE VERA LEAF; ARNICA MONTANA FLOWER; INDIAN FRANKINCENSE OIL; GREEN TEA LEAF; CARBOMER HOMOPOLYMER, UNSPECIFIED TYPE; CAMPHOR OIL; TURMERIC OIL; DIMETHYL SULFONE; GLYCYRRHIZINATE DIPOTASSIUM; ETHYLHEXYLGLYCERIN; EUCALYPTUS OIL; GLYCERIN; ISOPROPYL ALCOHOL; ARGININE; LIMONENE, (+)-; MAGNESIUM SULFATE, UNSPECIFIED FORM; TEA TREE OIL; MENTHA SPICATA OIL; NIACINAMIDE; ASIAN GINSENG; PHENOXYETHANOL; POLYSORBATE 20; .ALPHA.-TOCOPHEROL ACETATE; TROLAMINE; WATER; FD&C BLUE NO. 1

Mountain Ice Sports Recovery Gel

Active ingredients

Menthol 6%

Purpose

External Analgesic

Uses:

Temporary relief of minor aches and pains of muscles and joints associated with osteoarthritis, rheumatoid arthritis, muscle strains, and sprains.

Warnings:

For external use only.

Flammable: keep away from excessive heat or open flame. Avoid contact with eyes or mucous membranes.

When using this product:

- Do not apply to wounds, damaged skin, or irritated skin.
- Do not apply with other creams, ointments, sprays or liniments.

Stop use and ask a doctor if:

Conditions worsen, skin irritation develops, or condition does not improve after 7 days.

Keep out the reach of children.

If accidentally swallowed, seek medical attention immediately or contact Poison Control Center right away.

Directions:

Adults and children 2 years of age or older. Rub on the affected area evenly no more than 4 times per day. Children under 2 years of age: Consult with your doctor.

Inactive Ingredients:

Aloe Barbadensis Leaf Juice, Arnica Montana Flower Extract, Boswellia Serrata (Frankincense) Oil, Camellia Sinensis (Green Tea) Leaf Extract, Carbomer, Cinnamomum Camphora (camphor) Bark Oil, Curcuma Longa (Turmeric) Root Oil, Dimethyl Sulfone, Dipotassium Glycyrrhizate, Ethylhexylglycerin, Eucalyptus Globulus (Eucalyptus) Leaf Oil, Glycerin, Isopropyl Alcohol, L-Arginine, Limonene, Magnesium Sulfate, Melaleuca Alternifolia (Tea Tree) Leaf Oil, Mentha Spicata (Spearmint) Oil, Niacinamide, Panax Ginseng Root Extract, Phenoxyethanol, Polysorbate 20, Tocopheryl Acetate, Triethanolamine, Water (Aqua), Blue 1 (CI 42090).

Principal Display Panel

SPORT MUSCLE PAIN RELIEF THERAPY GEL

MOUNTAIN ICE

GINSENG, ARNICA, TURMERIC, VITAMIN B3, BOSWELLIA INDIAN FRANKINCENSE OIL, GREEN TEA EXTRACT, MSM, VITAMIN E, ALOE VERA, TEA TREE OIL, MENTHOL 6%, L-ARGININE AMINO ACID, LICORICE ROOT EXTRACT, EUCALYPTUS LEAF, SPEARMINT OIL
4 fl oz (118 ML)

Questions? 1-888-687-4334
Manufactured in the USA distributed by a Service-Disabled
Veteran-Owned Family Business Located in Upstate NY
Mountainside Medical Equipment Marcy, NY 13403

Label

Principal Display Panel

MUSCEL THERAPY GEL
MOUNTAIN ICESPORTS RECOVERY GEL

VEGAN
GLUTEN FREE \ ǀ / GLUTEN FREE \ ǀ /
MADE WITH NATURAL INGREDIENTS

MOUNTAIN ICE
3 FL OZ (99 ML)

Made in the USA by a Family Owned
Service-Disabled Veteran-owned
Small Business
Mountain Ice
9262 Old River Road
Marcy, NY 13403 USA
www.Mountain-Ice.com
If Pregnant or Breastfeeding: Ask
a health professional before use

Label